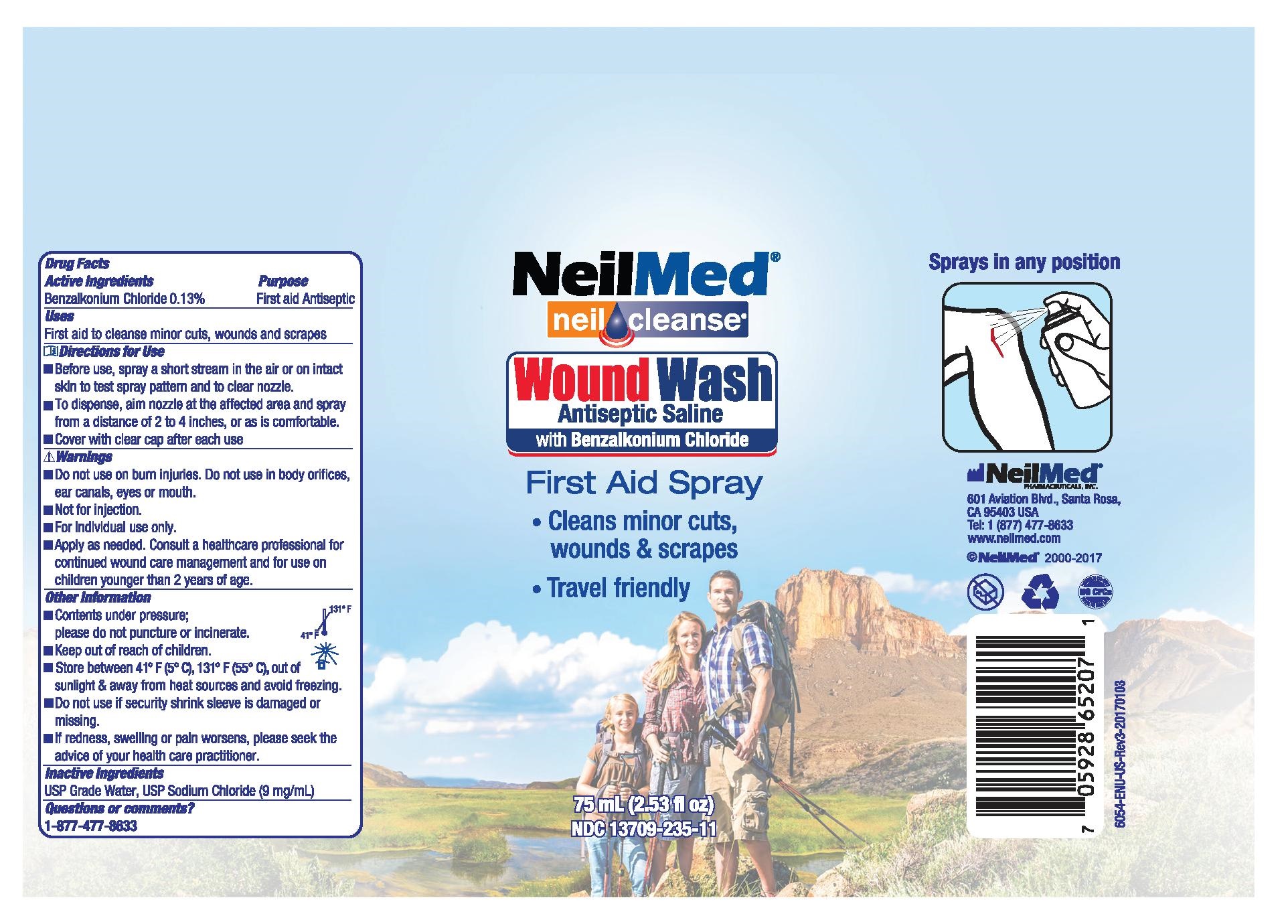 DRUG LABEL: Wound Wash Antiseptic Saline with Benzalkonium Chloride
NDC: 13709-235 | Form: AEROSOL, SPRAY
Manufacturer: NeilMed Pharmaceuticals, Inc.
Category: otc | Type: HUMAN OTC DRUG LABEL
Date: 20240111

ACTIVE INGREDIENTS: BENZALKONIUM CHLORIDE 1.3 mg/1 mL
INACTIVE INGREDIENTS: SODIUM CHLORIDE 9 mg/1 mL; WATER 89.7 mg/1 mL

Wound Wash Antiseptic Saline with Benzalkonium Chloride

Dosage and Administration

Before use, spray a short stream in the air or on intact skin to test spray pattern and to clear nozzle.

To dispense, aim nozzle at the affected area and spray from a distance of 2 to 4 inches, or as is comfortable.

Cover with clear cap after each use

Warnings

Do not use on burn injuries. Do not use in body orifices, ear canals, eyes or mouth.

Not for injection.

For individual use only.

Apply as needed. Consult a healthcare professional for continued wound care management and for use on children younger than 2 years of age.

Inactive Ingredients

USP Grade Water, USP Sodium Chloride (9mg/mL)

OTC Active Ingredient

Benzalkonium Chloride 0.13%

Indications and Usage

First Aid Antiseptic

First aid to cleanse minor cuts, wounds and scrapes

OTC- Purpose

First aid to cleanse minor cuts, wounds and scrapes

OTC- Keep Out of Reach of Children

Keep out of reach of children.